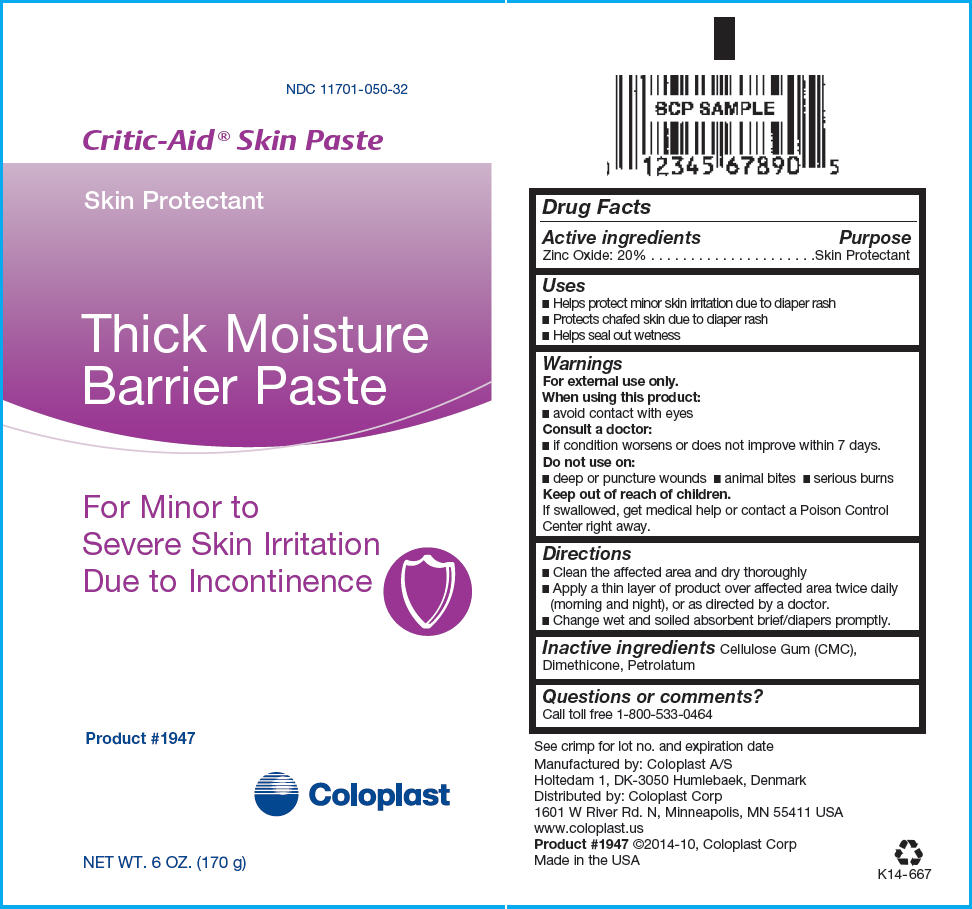 DRUG LABEL: Critic Aid Skin
NDC: 11701-050 | Form: PASTE
Manufacturer: Coloplast Manufacturing US, LLC
Category: otc | Type: HUMAN OTC DRUG LABEL
Date: 20231220

ACTIVE INGREDIENTS: ZINC OXIDE 200 mg/1 g
INACTIVE INGREDIENTS: PETROLATUM; DIMETHICONE; CROSCARMELLOSE SODIUM

Critic-Aid® Skin Paste

Drug Facts

Active ingredients

Zinc Oxide: 20%

Purpose

Skin Protectant

Uses

- Helps protect minor skin irritation due to diaper rash
- Protects chafed skin due to diaper rash
- Helps seal out wetness

Warnings

For external use only.

When using this product:

- avoid contact with eyes

Consult a doctor:

- if condition worsens or does not improve within 7 days.

Do not use on:

- deep or puncture wounds
- animal bites
- serious burns

Keep out of reach of children.

If swallowed, get medical help or contact a Poison Control Center right away.

Directions

- Clean the affected area and dry thoroughly
- Apply a thin layer of product over affected area twice daily (morning and night), or as directed by a doctor.
- Change wet and soiled absorbent brief/diapers promptly.

Inactive ingredients

Cellulose Gum (CMC), Dimethicone, Petrolatum

Questions or comments?

Call toll free 1-800-533-0464

Manufactured by: Coloplast A/S
Holtedam 1, DK-3050 Humlebaek, Denmark

Distributed by: Coloplast Corp
1601 W River Rd. N, Minneapolis, MN 55411 USA

PRINCIPAL DISPLAY PANEL - 170 g Tube Label

NDC 11701-050-32

Critic-Aid® Skin Paste

Skin Protectant

Thick Moisture
Barrier Paste

For Minor to
Severe Skin Irritation
Due to Incontinence

Product #1947

Coloplast

NET WT. 6 OZ. (170 g)